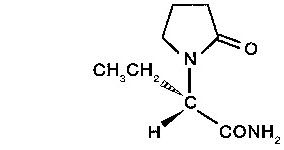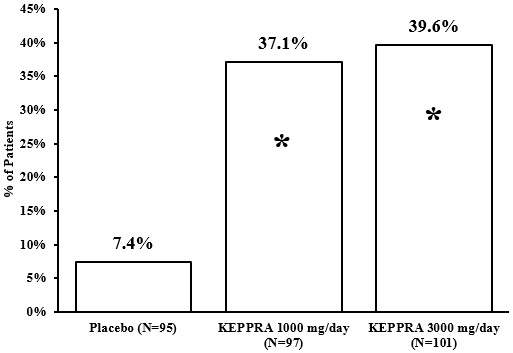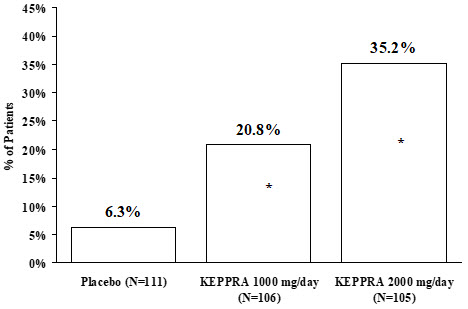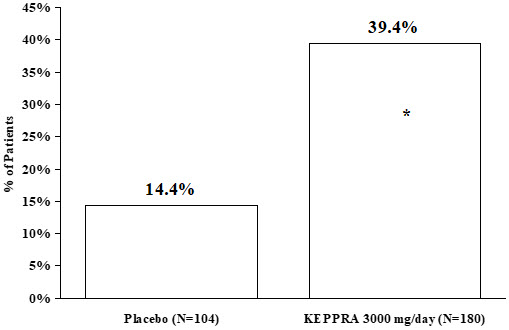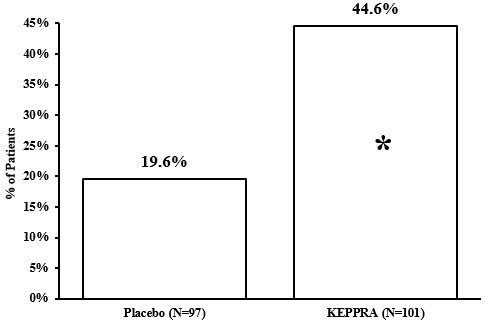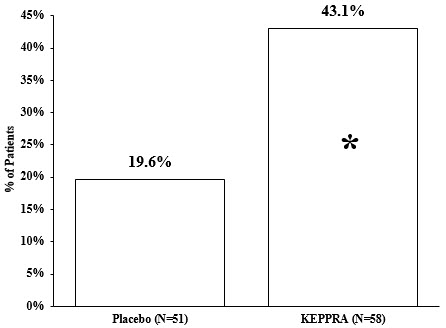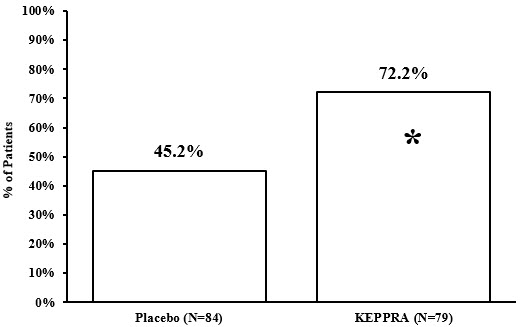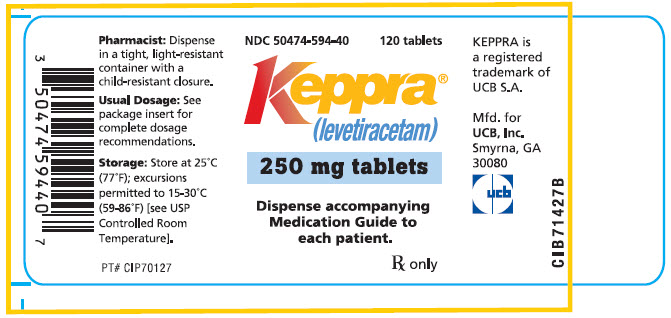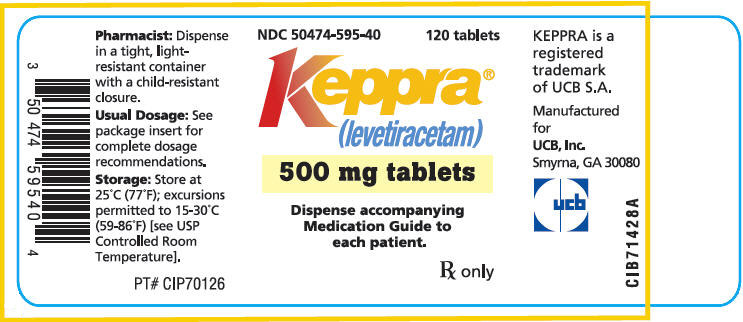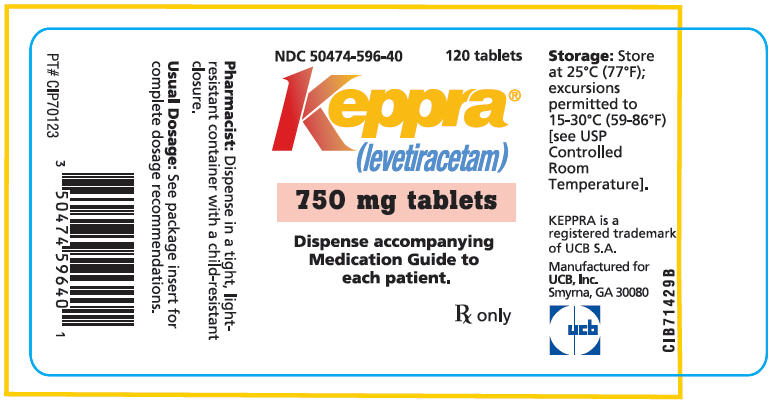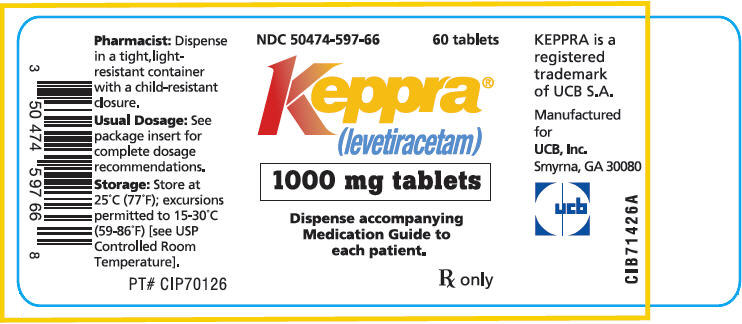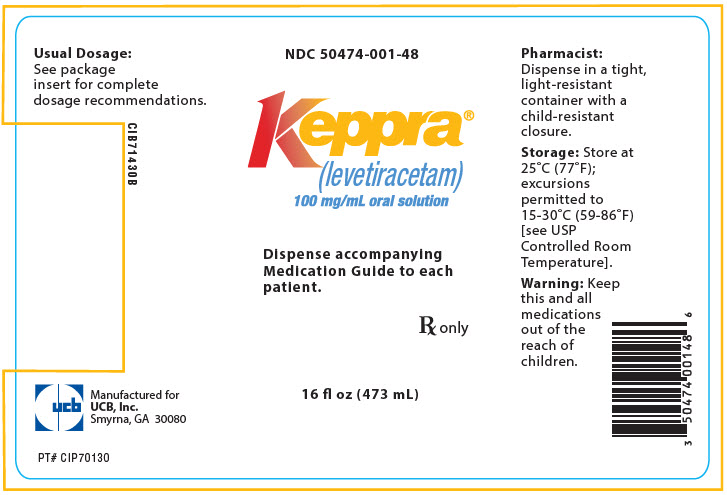 DRUG LABEL: Keppra
NDC: 50474-594 | Form: TABLET, FILM COATED
Manufacturer: UCB, Inc.
Category: prescription | Type: HUMAN PRESCRIPTION DRUG LABEL
Date: 20260128

ACTIVE INGREDIENTS: LEVETIRACETAM 250 mg/1 1
INACTIVE INGREDIENTS: INDIGOTINDISULFONATE SODIUM; ALUMINUM OXIDE; SILICON DIOXIDE; CROSCARMELLOSE SODIUM; MAGNESIUM STEARATE; POLYETHYLENE GLYCOL 3350; POLYETHYLENE GLYCOL 6000; POLYVINYL ALCOHOL, UNSPECIFIED; TALC; TITANIUM DIOXIDE; FD&C BLUE NO. 2

HIGHLIGHTS OF PRESCRIBING INFORMATION

These highlights do not include all the information needed to use KEPPRA®safely and effectively. See full prescribing information for KEPPRA.
KEPPRA (levetiracetam) tablets, for oral use
KEPPRA (levetiracetam) oral solution
Initial U.S. Approval: 1999

RECENT MAJOR CHANGES

Warnings and Precautions (5.6) | 3/2024

1 INDICATIONS AND USAGE

KEPPRA is indicated for the treatment of partial-onset seizures in patients 1 month of age and older (1.1)

KEPPRA is indicated for adjunctive therapy for the treatment of:

- Myoclonic seizures in patients 12 years of age and older with juvenile myoclonic epilepsy (1.2)
- Primary generalized tonic-clonic seizures in patients 6 years of age and older with idiopathic generalized epilepsy (1.3)

2 DOSAGE AND ADMINISTRATION

- Use the oral solution for pediatric patients with body weight ≤ 20 kg (2.1)
- For pediatric patients, use weight-based dosing for the oral solution with a calibrated measuring device (not a household teaspoon or tablespoon) (2.1)

Partial-Onset Seizures (monotherapy or adjunctive therapy)

- 1 Month to < 6 Months: 7 mg/kg twice daily; increase by 7 mg/kg twice daily every 2 weeks to recommended dose of 21 mg/kg twice daily (2.2)
- 6 Months to < 4 Years: 10 mg/kg twice daily; increase by 10 mg/kg twice daily every 2 weeks to recommended dose of 25 mg/kg twice daily (2.2)
- 4 Years to < 16 Years: 10 mg/kg twice daily; increase by 10 mg/kg twice daily every 2 weeks to recommended dose of 30 mg/kg twice daily (2.2)
- Adults 16 Years and Older: 500 mg twice daily; increase by 500 mg twice daily every 2 weeks to a recommended dose of 1500 mg twice daily (2.2)

Myoclonic Seizures in Adults and Pediatric Patients 12 Years and Older

- 500 mg twice daily; increase by 500 mg twice daily every 2 weeks to recommended dose of 1500 mg twice daily (2.3)

Primary Generalized Tonic-Clonic Seizures

- 6 Years to < 16 Years: 10 mg/kg twice daily, increase in increments of 10 mg/kg twice daily every 2 weeks to recommended dose of 30 mg/kg twice daily (2.4)
- Adults 16 Years and Older: 500 mg twice daily, increase by 500 mg twice daily every 2 weeks to recommended dose of 1500 mg twice daily (2.4)

Adult Patients with Impaired Renal Function

- Dose adjustment is recommended, based on the patient's estimated creatinine clearance (2.5, 8.6)

3 DOSAGE FORMS AND STRENGTHS

- 250 mg, 500 mg, 750 mg, and 1000 mg film-coated, scored tablets (3)
- 100 mg/mL solution (3)

4 CONTRAINDICATIONS

Known hypersensitivity to levetiracetam; angioedema and anaphylaxis have occurred (4, 5.4)

5 WARNINGS AND PRECAUTIONS

- Behavioral abnormalities including psychotic symptoms, suicidal ideation, irritability, and aggressive behavior have been observed; monitor patients for psychiatric signs and symptoms (5.1)
- Suicidal Behavior and Ideation: Monitor patients for new or worsening depression, suicidal thoughts/behavior, and/or unusual changes in mood or behavior (5.2)
- Monitor for somnolence and fatigue and advise patients not to drive or operate machinery until they have gained sufficient experience on KEPPRA (5.3)
- Serious Dermatological Reactions: Discontinue KEPPRA at the first sign of rash unless clearly not drug related (5.5)
- Drug Reaction with Eosinophilia and Systemic Symptoms (DRESS)/Multiorgan Hypersensitivity: Discontinue if no alternative etiology (5.6)
- Coordination Difficulties: Monitor for ataxia, abnormal gait, and incoordination. Advise patients to not drive or operate machinery until they have gained experience on KEPPRA (5.7)
- Withdrawal Seizures: KEPPRA must be gradually withdrawn (5.8)

6 ADVERSE REACTIONS

Most common adverse reactions (incidence ≥ 5% more than placebo) include:

- Adult patients: somnolence, asthenia, infection and dizziness (6.1)
- Pediatric patients: fatigue, aggression, nasal congestion, decreased appetite, and irritability (6.1)

To report SUSPECTED ADVERSE REACTIONS, contact UCB, Inc. at 1-844-599-2273 or FDA at 1-800-FDA-1088 or www.fda.gov/medwatch.

8 USE IN SPECIFIC POPULATIONS

Pregnancy: Plasma levels of levetiracetam may be decreased and therefore need to be monitored closely during pregnancy. Based on animal data, may cause fetal harm (5.11, 8.1)

FULL PRESCRIBING INFORMATION

1 INDICATIONS AND USAGE

1.1 Partial-Onset Seizures

KEPPRA is indicated for the treatment of partial-onset seizures in patients 1 month of age and older.

1.2 Myoclonic Seizures in Patients with Juvenile Myoclonic Epilepsy

KEPPRA is indicated as adjunctive therapy for the treatment of myoclonic seizures in patients 12 years of age and older with juvenile myoclonic epilepsy.

1.3 Primary Generalized Tonic-Clonic Seizures

KEPPRA is indicated as adjunctive therapy for the treatment of primary generalized tonic-clonic seizures in patients 6 years of age and older with idiopathic generalized epilepsy.

2 DOSAGE AND ADMINISTRATION

2.1 Important Administration Instructions

KEPPRA is given orally with or without food. The KEPPRA dosing regimen depends on the indication, age group, dosage form (tablets or oral solution), and renal function.

Prescribe the oral solution for pediatric patients with body weight ≤ 20 kg. Prescribe the oral solution or tablets for pediatric patients with body weight above 20 kg.

When using the oral solution in pediatric patients, dosing is weight-based (mg per kg) using a calibrated measuring device (not a household teaspoon or tablespoon).

KEPPRA tablets should be swallowed whole. KEPPRA tablets should not be chewed or crushed.

2.2 Dosing for Partial-Onset Seizures

The recommended dosing for monotherapy and adjunctive therapy is the same; as outlined below.

Adults 16 Years of Age and Older

Initiate treatment with a daily dose of 1000 mg/day, given as twice-daily dosing (500 mg twice daily). Additional dosing increments may be given (1000 mg/day additional every 2 weeks) to a maximum recommended daily dose of 3000 mg. There is no evidence that doses greater than 3000 mg/day confer additional benefit.

Pediatric Patients

1 Month to < 6 Months

Initiate treatment with a daily dose of 14 mg/kg in 2 divided doses (7 mg/kg twice daily). Increase the daily dose every 2 weeks by increments of 14 mg/kg to the recommended daily dose of 42 mg/kg (21 mg/kg twice daily). In the clinical trial, the mean daily dose was 35 mg/kg in this age group.

6 Months to < 4 Years:

Initiate treatment with a daily dose of 20 mg/kg in 2 divided doses (10 mg/kg twice daily). Increase the daily dose in 2 weeks by an increment of 20 mg/kg to the recommended daily dose of 50 mg/kg (25 mg/kg twice daily). If a patient cannot tolerate a daily dose of 50 mg/kg, the daily dose may be reduced. In the clinical trial, the mean daily dose was 47 mg/kg in this age group.

4 Years to < 16 Years

Initiate treatment with a daily dose of 20 mg/kg in 2 divided doses (10 mg/kg twice daily). Increase the daily dose every 2 weeks by increments of 20 mg/kg to the recommended daily dose of 60 mg/kg (30 mg/kg twice daily). If a patient cannot tolerate a daily dose of 60 mg/kg, the daily dose may be reduced. In the clinical trial, the mean daily dose was 44 mg/kg. The maximum daily dose was 3000 mg/day.

For KEPPRA tablet dosing in pediatric patients weighing 20 to 40 kg, initiate treatment with a daily dose of 500 mg given as twice daily dosing (250 mg twice daily). Increase the daily dose every 2 weeks by increments of 500 mg to a maximum recommended daily dose of 1500 mg (750 mg twice daily).

For KEPPRA tablet dosing in pediatric patients weighing more than 40 kg, initiate treatment with a daily dose of 1000 mg/day given as twice daily dosing (500 mg twice daily). Increase the daily dose every 2 weeks by increments of 1000 mg/day to a maximum recommended daily dose of 3000 mg (1500 mg twice daily).

KEPPRA Oral Solution Weight-Based Dosing Calculation For Pediatric Patients

The following calculation should be used to determine the appropriate daily dose of oral solution for pediatric patients:

Total daily dose (mL/day) = | Daily dose (mg/kg/day) × patient weight (kg) ------------------------------------------------ 100 mg/mL

2.3 Dosing for Myoclonic Seizures in Patients 12 Years of Age and Older with Juvenile Myoclonic Epilepsy

Initiate treatment with a dose of 1000 mg/day, given as twice-daily dosing (500 mg twice daily). Increase the dosage by 1000 mg/day every 2 weeks to the recommended daily dose of 3000 mg. The effectiveness of doses lower than 3000 mg/day has not been studied.

2.4 Dosing for Primary Generalized Tonic-Clonic Seizures

Adults 16 Years of Age and Older

Initiate treatment with a dose of 1000 mg/day, given as twice-daily dosing (500 mg twice daily). Increase dosage by 1000 mg/day every 2 weeks to the recommended daily dose of 3000 mg. The effectiveness of doses lower than 3000 mg/day has not been adequately studied.

Pediatric Patients 6 to <16 Years of Age

Initiate treatment with a daily dose of 20 mg/kg in 2 divided doses (10 mg/kg twice daily). Increase the daily dose every 2 weeks by increments of 20 mg/kg to the recommended daily dose of 60 mg/kg (30 mg/kg twice daily). The effectiveness of doses lower than 60 mg/kg/day has not been adequately studied. Patients with body weight ≤20 kg should be dosed with oral solution. Patients with body weight above 20 kg can be dosed with either tablets or oral solution [see Dosage and Administration (2.1)] . Only whole tablets should be administered.

2.5 Dosage Adjustments in Adult Patients with Renal Impairment

KEPPRA dosing must be individualized according to the patient's renal function status. Recommended dosage adjustments for adults are shown in Table 1. In order to calculate the dose recommended for patients with renal impairment, creatinine clearance adjusted for body surface area must be calculated. To do this an estimate of the patient's creatinine clearance (CLcr) in mL/min must first be calculated using the following formula:

CLcr= | [140-age (years)] × weight (kg) ---------------------------------------- 72 × serum creatinine (mg/dL) | (× 0.85 for female patients)

Then CLcr is adjusted for body surface area (BSA) as follows:

CLcr (mL/min/1.73m^2)= | CLcr (mL/min) ------------------------------ BSA subject (m^2) | × 1.73

Table 1: Dosing Adjustment Regimen for Adult Patients with Renal Impairment
Group | Creatinine Clearance (mL/min/1.73m^2) | Dosage (mg) | Frequency
Normal | > 80 | 500 to 1,500 | Every 12 hours
Mild | 50 – 80 | 500 to 1,000 | Every 12 hours
Moderate | 30 – 50 | 250 to 750 | Every 12 hours
Severe | < 30 | 250 to 500 | Every 12 hours
ESRD patients using dialysis | ---- | 500 to 1,000 [Following dialysis, a 250 to 500 mg supplemental dose is recommended.] | Every 24 hours

2.6 Discontinuation of KEPPRA

Avoid abrupt withdrawal from KEPPRA in order to reduce the risk of increased seizure frequency and status epilepticus [see Warnings and Precautions (5.8)].

3 DOSAGE FORMS AND STRENGTHS

KEPPRA Tablets

- 250 mg: blue, oblong-shaped, scored, film-coated, and debossed with "ucb 250" on one side
- 500 mg: yellow, oblong-shaped, scored, film-coated, and debossed with "ucb 500" on one side
- 750 mg: orange, oblong-shaped, scored, film-coated, and debossed with "ucb 750" on one side
- 1000 mg: white, oblong-shaped, scored, film-coated, and debossed with "ucb 1000" on one side

KEPPRA Oral Solution

- 100 mg/mL: a clear, colorless, grape-flavored liquid

4 CONTRAINDICATIONS

KEPPRA is contraindicated in patients with a hypersensitivity to levetiracetam .Reactions have included anaphylaxis and angioedema [see Warnings and Precautions (5.4)] .

5 WARNINGS AND PRECAUTIONS

5.1 Behavioral Abnormalities and Psychotic Symptoms

KEPPRA may cause behavioral abnormalities and psychotic symptoms. Patients treated with KEPPRA should be monitored for psychiatric signs and symptoms.

Behavioral abnormalities

In clinical studies, 13% of adult KEPPRA-treated patients and 38% of pediatric KEPPRA-treated patients (4 to 16 years of age) compared to 6% and 19% of adult and pediatric placebo-treated patients, experienced non-psychotic behavioral symptoms (reported as aggression, agitation, anger, anxiety, apathy, depersonalization, depression, emotional lability, hostility, hyperkinesias, irritability, nervousness, neurosis, and personality disorder).

A randomized double-blind, placebo-controlled study was performed to assess the neurocognitive and behavioral effects of KEPPRA as adjunctive therapy in pediatric patients (4 to 16 years of age). The results from an exploratory analysis indicated a worsening in KEPPRA-treated patients on aggressive behavior (one of eight behavior dimensions) as measured in a standardized and systematic way using a validated instrument, the Achenbach Child Behavior Checklist (CBCL/6-18).

In clinical studies in pediatric patients 1 month to < 4 years of age, irritability was reported in 12% of the KEPPRA-treated patients compared to 0% of placebo-treated patients.

In clinical studies, 1.7% of adult KEPPRA-treated patients discontinued treatment due to behavioral adverse reactions, compared to 0.2% of placebo-treated patients. The treatment dose was reduced in 0.8% of adult KEPPRA-treated patients and in 0.5% of placebo-treated patients. Overall, 11% of KEPPRA-treated pediatric patients experienced behavioral symptoms associated with discontinuation or dose reduction, compared to 6% of placebo-treated patients.

Psychotic symptoms

In clinical studies, 1% of KEPPRA-treated adult patients, 2% of KEPPRA-treated pediatric patients 4 to 16 years of age, and 17% of KEPPRA-treated pediatric patients 1 month to <4 years of age experienced psychotic symptoms, compared to 0.2%, 2%, and 5% in the corresponding age groups treated with placebo. In a controlled study that assessed the neurocognitive and behavioral effects of KEPPRA in pediatric patients 4 to 16 years of age, 1.6% of KEPPRA-treated patients experienced paranoia, compared to 0% of placebo-treated patients. In the same study, 3.1% of KEPPRA-treated patients experienced confusional state, compared to 0% of placebo-treated patients [see Use in Specific Populations (8.4)] .

In clinical studies, two (0.3%) KEPPRA-treated adult patients were hospitalized and their treatment was discontinued due to psychosis. Both events, reported as psychosis, developed within the first week of treatment and resolved within 1 to 2 weeks following treatment discontinuation. There was no difference between drug and placebo-treated patients in the incidence of the pediatric patients who discontinued treatment due to psychotic and non-psychotic adverse reactions.

5.2 Suicidal Behavior and Ideation

Antiepileptic drugs (AEDs), including KEPPRA, increase the risk of suicidal thoughts or behavior in patients taking these drugs for any indication. Patients treated with any AED for any indication should be monitored for the emergence or worsening of depression, suicidal thoughts or behavior, and/or any unusual changes in mood or behavior.

Pooled analyses of 199 placebo-controlled clinical trials (mono- and adjunctive therapy) of 11 different AEDs showed that patients randomized to one of the AEDs had approximately twice the risk (adjusted Relative Risk 1.8, 95% CI:1.2, 2.7) of suicidal thinking or behavior compared to patients randomized to placebo. In these trials, which had a median treatment duration of 12 weeks, the estimated incidence rate of suicidal behavior or ideation among 27,863 AED-treated patients was 0.43%, compared to 0.24% among 16,029 placebo-treated patients, representing an increase of approximately one case of suicidal thinking or behavior for every 530 patients treated. There were four suicides in drug-treated patients in the trials and none in placebo-treated patients, but the number is too small to allow any conclusion about drug effect on suicide.

The increased risk of suicidal thoughts or behavior with AEDs was observed as early as one week after starting drug treatment with AEDs and persisted for the duration of treatment assessed. Because most trials included in the analysis did not extend beyond 24 weeks, the risk of suicidal thoughts or behavior beyond 24 weeks could not be assessed.

The risk of suicidal thoughts or behavior was generally consistent among drugs in the data analyzed. The finding of increased risk with AEDs of varying mechanisms of action and across a range of indications suggests that the risk applies to all AEDs used for any indication. The risk did not vary substantially by age (5-100 years) in the clinical trials analyzed. Table 2 shows absolute and relative risk by indication for all evaluated AEDs.

Table 2: Risk by Indication for Antiepileptic Drugs in the Pooled Analysis
Indication | Placebo Patients with Events Per 1000 Patients | Drug Patients with Events Per 1000 Patients | Relative Risk: Incidence of Events in Drug Patients/Incidence in Placebo Patients | Risk Difference: Additional Drug Patients with Events Per 1000 Patients
Epilepsy | 1.0 | 3.4 | 3.5 | 2.4
Psychiatric | 5.7 | 8.5 | 1.5 | 2.9
Other | 1.0 | 1.8 | 1.9 | 0.9
Total | 2.4 | 4.3 | 1.8 | 1.9

The relative risk for suicidal thoughts or behavior was higher in clinical trials for epilepsy than in clinical trials for psychiatric or other conditions, but the absolute risk differences were similar for the epilepsy and psychiatric indications.

Anyone considering prescribing KEPPRA or any other AED must balance the risk of suicidal thoughts or behaviors with the risk of untreated illness. Epilepsy and many other illnesses for which AEDs are prescribed are themselves associated with morbidity and mortality and an increased risk of suicidal thoughts and behavior. Should suicidal thoughts and behavior emerge during treatment, the prescriber needs to consider whether the emergence of these symptoms in any given patient may be related to the illness being treated.

5.3 Somnolence and Fatigue

KEPPRA may cause somnolence and fatigue. Patients should be monitored for these signs and symptoms and advised not to drive or operate machinery until they have gained sufficient experience on KEPPRA to gauge whether it adversely affects their ability to drive or operate machinery.

Somnolence

In controlled trials of adult patients with epilepsy experiencing partial-onset seizures, 15% of KEPPRA-treated patients reported somnolence, compared to 8% of placebo-treated patients. There was no clear dose response up to 3000 mg/day. In a study where there was no titration, about 45% of patients receiving 4000 mg/day reported somnolence. The somnolence was considered serious in 0.3% of KEPPRA-treated patients, compared to 0% in the placebo group. About 3% of KEPPRA-treated patients discontinued treatment due to somnolence, compared to 0.7% of placebo-treated patients. In 1.4% of KEPPRA-treated patients and 0.9% of placebo-treated patients, the dose was reduced, while 0.3% of the KEPPRA-treated patients were hospitalized due to somnolence.

Asthenia

In controlled clinical studies of adult patients with epilepsy experiencing partial-onset seizures, 15% of KEPPRA-treated patients reported asthenia, compared to 9% of placebo-treated patients. Treatment was discontinued due to asthenia in 0.8% of KEPPRA-treated patients as compared to 0.5% of placebo-treated patients. In 0.5% of KEPPRA-treated patients and in 0.2% of placebo-treated patients, the dose was reduced due to asthenia.

Somnolence and asthenia occurred most frequently within the first 4 weeks of treatment. In general, the incidences of somnolence and fatigue in the pediatric partial-onset seizure studies, and in pediatric and adult myoclonic and primary generalized tonic-clonic seizure studies were comparable to those of the adult partial-onset seizure studies.

5.4 Anaphylaxis and Angioedema

KEPPRA can cause anaphylaxis or angioedema after the first dose or at any time during treatment. Signs and symptoms in cases reported in the postmarketing setting have included hypotension, hives, rash, respiratory distress, and swelling of the face, lip, mouth, eye, tongue, throat, and feet. In some reported cases, reactions were life-threatening and required emergency treatment. If a patient develops signs or symptoms of anaphylaxis or angioedema, KEPPRA should be discontinued and the patient should seek immediate medical attention. KEPPRA should be discontinued permanently if a clear alternative etiology for the reaction cannot be established [see Contraindications (4)] .

5.5 Serious Dermatological Reactions

Serious dermatological reactions, including Stevens-Johnson syndrome (SJS) and toxic epidermal necrolysis (TEN), have been reported in both pediatric and adult patients treated with KEPPRA. The median time of onset is reported to be 14 to 17 days, but cases have been reported at least four months after initiation of treatment. Recurrence of the serious skin reactions following rechallenge with KEPPRA has also been reported. KEPPRA should be discontinued at the first sign of a rash, unless the rash is clearly not drug-related. If signs or symptoms suggest SJS/TEN, use of this drug should not be resumed and alternative therapy should be considered.

5.6 Drug Reaction with Eosinophilia and Systemic Symptoms (DRESS)/Multiorgan Hypersensitivity

Drug Reaction with Eosinophilia and Systemic Symptoms (DRESS), also known as multiorgan hypersensitivity, has been reported in patients taking antiepileptic drugs, including KEPPRA. These events can be fatal or life-threatening, particularly if diagnosis and treatment do not occur as early as possible. DRESS typically, although not exclusively, presents with fever, rash, lymphadenopathy, and/or facial swelling, in association with other organ system involvement, such as hepatitis, nephritis, hematological abnormalities, myocarditis, or myositis, sometimes resembling an acute viral infection. Eosinophilia is often present. Because this disorder is variable in its expression, other organ systems not noted here may be involved. It is important to note that early manifestations of hypersensitivity, such as fever or lymphadenopathy, may be present even though rash is not evident. If such signs or symptoms are present, the patient should be evaluated immediately. KEPPRA should be discontinued if an alternative etiology for the signs or symptoms cannot be established [see Contraindications (4)] .

5.7 Coordination Difficulties

KEPPRA may cause coordination difficulties.

In controlled clinical studies in adult patients with partial-onset seizure studies, 3.4% of adult KEPPRA-treated patients experienced coordination difficulties, (reported as either ataxia, abnormal gait, or incoordination) compared to 1.6% of placebo-treated patients. A total of 0.4% of patients in controlled clinical studies discontinued KEPPRA treatment due to ataxia, compared to 0% of placebo-treated patients. In 0.7% of KEPPRA-treated patients and in 0.2% of placebo-treated patients, the dose was reduced due to coordination difficulties, while one of the KEPPRA-treated patients was hospitalized due to worsening of pre-existing ataxia. These events occurred most frequently within the first 4 weeks of treatment.

Patients should be monitored for these signs and symptoms and advised not to drive or operate machinery until they have gained sufficient experience on KEPPRA to gauge whether it could adversely affect their ability to drive or operate machinery.

5.8 Withdrawal Seizures

As with most antiepileptic drugs, KEPPRA should generally be withdrawn gradually because of the risk of increased seizure frequency and status epilepticus. If withdrawal is needed because of a serious adverse reaction, rapid discontinuation can be considered.

5.9 Hematologic Abnormalities

KEPPRA can cause hematologic abnormalities. Hematologic abnormalities occurred in clinical trials and included decreases in white blood cell (WBC), neutrophil, and red blood cell (RBC) counts; decreases in hemoglobin and hematocrit; and increases in eosinophil counts. Cases of agranulocytosis, pancytopenia, and thrombocytopenia have been reported in the postmarketing setting. A complete blood count is recommended in patients experiencing significant weakness, pyrexia, recurrent infections, or coagulation disorders.

Partial-Onset Seizures

Adults

Minor, but statistically significant, decreases compared to placebo in total mean RBC count (0.03 × 106/mm3), mean hemoglobin (0.09 g/dL), and mean hematocrit (0.38%), were seen in KEPPRA-treated patients in controlled trials.

A total of 3.2% of KEPPRA-treated and 1.8% of placebo-treated patients had at least one possibly significant (≤2.8 × 10^9/L) decreased WBC, and 2.4% of KEPPRA-treated and 1.4% of placebo-treated patients had at least one possibly significant (≤1.0 × 10^9/L) decreased neutrophil count. Of the KEPPRA-treated patients with a low neutrophil count, all but one rose towards or to baseline with continued treatment. No patient was discontinued secondary to low neutrophil counts.

Pediatric Patients 4 Years to < 16 Years

Statistically significant decreases in WBC and neutrophil counts were seen in KEPPRA-treated patients as compared to placebo. The mean decreases from baseline in the KEPPRA-treated group were -0.4 × 10^9/L and -0.3 × 10^9/L, respectively, whereas there were small increases in the placebo group. Mean relative lymphocyte counts increased by 1.7% in KEPPRA-treated patients, compared to a decrease of 4% in placebo patients (statistically significant).

In the controlled trial, more KEPPRA-treated patients had a possibly clinically significant abnormally low WBC value (3% of KEPPRA-treated patients versus 0% of placebo-treated patients), however, there was no apparent difference between treatment groups with respect to neutrophil count (5% of KEPPRA-treated patients versus 4.2% of placebo-treated patients). No patient was discontinued secondary to low WBC or neutrophil counts.

In the controlled cognitive and neuropsychological safety study, 5 patients (8.6%) in the KEPPRA-treated group and two patients (6.1%) in the placebo-treated group had high eosinophil count values that were possibly clinically significant (≥10% or ≥0.7 × 10^9/L).

5.10 Increase in Blood Pressure

In a randomized, placebo-controlled study in patients 1 month to <4 years of age, a significantly higher risk of increased diastolic blood pressure was observed in the KEPPRA-treated patients (17%), compared to the placebo-treated patients (2%). There was no overall difference in mean diastolic blood pressure between the treatment groups. This disparity between the KEPPRA and placebo treatment groups was not observed in the studies of older children or in adults.

Monitor patients 1 month to <4 years of age for increases in diastolic blood pressure.

5.11 Seizure Control During Pregnancy

Physiological changes may gradually decrease plasma levels of levetiracetam throughout pregnancy. This decrease is more pronounced during the third trimester. It is recommended that patients be monitored carefully during pregnancy. Close monitoring should continue through the postpartum period especially if the dose was changed during pregnancy.

6 ADVERSE REACTIONS

The following adverse reactions are discussed in more details in other sections of labeling:

- Behavior Abnormalities and Psychotic Symptoms [see Warnings and Precautions (5.1)]
- Suicidal Behavior and Ideation [see Warnings and Precautions (5.2)]
- Somnolence and Fatigue [see Warnings and Precautions (5.3)]
- Anaphylaxis and Angioedema [see Warnings and Precautions (5.4)]
- Serious Dermatological Reactions [see Warnings and Precautions (5.5)]
- Drug Reaction with Eosinophilia and Systemic Symptoms (DRESS)/Multiorgan Hypersensitivity [see
- Warnings and Precautions (5.6)]
- Coordination Difficulties [see Warnings and Precautions (5.7)]
- Hematologic Abnormalities [see Warnings and Precautions (5.9)]
- Increase in Blood Pressure [see Warnings and Precautions (5.10)]

6.1 Clinical Trials Experience

Because clinical trials are conducted under widely varying conditions, adverse reaction rates observed in the clinical trials of a drug cannot be directly compared to rates in the clinical trials of another drug and may not reflect the rates observed in practice.

Partial-Onset Seizures

Adults

In controlled clinical studies in adults with partial-onset seizures [see Clinical Studies (14.1)] , the most common adverse reactions in patients receiving KEPPRA in combination with other AEDs, for events with rates greater than placebo, were somnolence, asthenia, infection, and dizziness. Of the most common adverse reactions in adults experiencing partial-onset seizures, asthenia, somnolence, and dizziness occurred predominantly during the first 4 weeks of treatment with KEPPRA.

Table 3 lists adverse reactions that occurred in at least 1% of adult epilepsy patients receiving KEPPRA in placebo-controlled studies and were numerically more common than in patients treated with placebo. In these studies, either KEPPRA or placebo was added to concurrent AED therapy.

Table 3: Adverse Reactions in Pooled Placebo-Controlled, Adjunctive Studies in Adults Experiencing Partial-Onset Seizures
 | KEPPRA (N=769) % | Placebo (N=439) %
Asthenia | 15 | 9
Somnolence | 15 | 8
Headache | 14 | 13
Infection | 13 | 8
Dizziness | 9 | 4
Pain | 7 | 6
Pharyngitis | 6 | 4
Depression | 4 | 2
Nervousness | 4 | 2
Rhinitis | 4 | 3
Anorexia | 3 | 2
Ataxia | 3 | 1
Vertigo | 3 | 1
Amnesia | 2 | 1
Anxiety | 2 | 1
Cough Increased | 2 | 1
Diplopia | 2 | 1
Emotional Lability | 2 | 0
Hostility | 2 | 1
Paresthesia | 2 | 1
Sinusitis | 2 | 1

In controlled adult clinical studies, 15% of patients receiving KEPPRA and 12% receiving placebo either discontinued or had a dose reduction as a result of an adverse reaction. Table 4 lists the most common (>1%) adverse reactions that resulted in discontinuation or dose reduction and that occurred more frequently in KEPPRA-treated patients than in placebo-treated patients.

Table 4: Adverse Reactions that Resulted in Discontinuation or Dose Reduction in Placebo-Controlled Studies in Adult Patients Experiencing Partial-Onset Seizures
Adverse Reaction | KEPPRA (N=769) % | Placebo (N=439) %
Somnolence | 4 | 2
Dizziness | 1 | 0

Pediatric Patients 4 Years to <16 Years

The adverse reaction data presented below was obtained from a pooled analysis of two controlled pediatric clinical studies in pediatric patients 4 to 16 years of age with partial-onset seizures. The most common adverse reactions in pediatric patients receiving KEPPRA in combination with other AEDs, for events with rates greater than placebo, were fatigue, aggression, nasal congestion, decreased appetite, and irritability.

Table 5 lists adverse reactions from the pooled pediatric controlled studies (4 to 16 years of age) that occurred in at least 2% of pediatric KEPPRA-treated patients and were numerically more common than in pediatric patients treated with placebo. In these studies, either KEPPRA or placebo was added to concurrent AED therapy.

Table 5: Adverse Reactions in Pooled Placebo-Controlled, Adjunctive Studies in Pediatric Patients Ages 4 to 16 Years Experiencing Partial-Onset Seizures
 | KEPPRA (N=165) % | Placebo (N=131) %
Headache | 19 | 15
Nasopharyngitis | 15 | 12
Vomiting | 15 | 12
Somnolence | 13 | 9
Fatigue | 11 | 5
Aggression | 10 | 5
Cough | 9 | 5
Nasal Congestion | 9 | 2
Upper Abdominal Pain | 9 | 8
Decreased Appetite | 8 | 2
Abnormal Behavior | 7 | 4
Dizziness | 7 | 5
Irritability | 7 | 1
Pharyngolaryngeal Pain | 7 | 4
Diarrhea | 6 | 2
Lethargy | 6 | 5
Insomnia | 5 | 3
Agitation | 4 | 1
Anorexia | 4 | 3
Head Injury | 4 | 0
Altered Mood | 3 | 1
Constipation | 3 | 1
Contusion | 3 | 1
Depression | 3 | 1
Fall | 3 | 2
Influenza | 3 | 1
Affect Lability | 2 | 1
Anxiety | 2 | 1
Arthralgia | 2 | 0
Confusional State | 2 | 0
Conjunctivitis | 2 | 0
Ear Pain | 2 | 1
Gastroenteritis | 2 | 0
Joint Sprain | 2 | 1
Mood Swings | 2 | 1
Neck Pain | 2 | 1
Rhinitis | 2 | 0
Sedation | 2 | 1

In the controlled pooled pediatric clinical studies in patients 4-16 years of age, 7% of patients receiving KEPPRA and 9% receiving placebo discontinued as a result of an adverse reaction.

Pediatric Patients 1 Month to < 4 Years

In the 7-day, controlled pediatric clinical study in children 1 month to less than 4 years of age with partial-onset seizures, the most common adverse reactions in patients receiving KEPPRA in combination with other AEDs, for events with rates greater than placebo, were somnolence and irritability. Because of the shorter exposure period, incidences of adverse reactions are expected to be lower than in other pediatric studies in older patients. Therefore, other controlled pediatric data, presented above, should also be considered to apply to this age group.

Table 6 lists adverse reactions that occurred in at least 5% of pediatric epilepsy patients (ages 1 month to < 4 years) treated with KEPPRA in the placebo-controlled study and were numerically more common than in patients treated with placebo. In this study, either KEPPRA or placebo was added to concurrent AED therapy.

Table 6: Adverse Reactions in a Placebo-Controlled, Adjunctive Study in Pediatric Patients Ages 1 Month to < 4 Years Experiencing Partial-Onset Seizures
 | KEPPRA (N=60) % | Placebo (N=56) %
Somnolence | 13 | 2
Irritability | 12 | 0

In the 7-day controlled pediatric clinical study in patients 1 month to < 4 years of age, 3% of patients receiving KEPPRA and 2% receiving placebo either discontinued or had a dose reduction as a result of an adverse reaction. There was no adverse reaction that resulted in discontinuation for more than one patient.

Myoclonic Seizures

Although the pattern of adverse reactions in this study seems somewhat different from that seen in patients with partial-onset seizures, this is likely due to the much smaller number of patients in this study compared to partial seizure studies. The adverse reaction pattern for patients with JME is expected to be essentially the same as for patients with partial seizures.

In the controlled clinical study in patients 12 years of age and older with myoclonic seizures [see Clinical Studies (14.2)], the most common adverse reactions in patients receiving KEPPRA in combination with other AEDs, for events with rates greater than placebo, were somnolence, neck pain, and pharyngitis.

Table 7 lists adverse reactions that occurred in at least 5% of juvenile myoclonic epilepsy patients experiencing myoclonic seizures treated with KEPPRA and were numerically more common than in patients treated with placebo. In this study, either KEPPRA or placebo was added to concurrent AED therapy.

Table 7: Adverse Reactions in a Placebo-Controlled, Adjunctive Study in Patients 12 Years of Age and Older with Myoclonic Seizures
 | KEPPRA (N=60) % | Placebo (N=60) %
Somnolence | 12 | 2
Neck pain | 8 | 2
Pharyngitis | 7 | 0
Depression | 5 | 2
Influenza | 5 | 2
Vertigo | 5 | 3

In the placebo-controlled study, 8% of patients receiving KEPPRA and 2% receiving placebo either discontinued or had a dose reduction as a result of an adverse reaction. The adverse reactions that led to discontinuation or dose reduction and that occurred more frequently in KEPPRA-treated patients than in placebo-treated patients are presented in Table 8.

Table 8: Adverse Reactions that Resulted in Discontinuation or Dose Reduction in a Placebo-Controlled Study in Patients with Juvenile Myoclonic Epilepsy
Adverse Reaction | KEPPRA (N=60) % | Placebo (N=60) %
Anxiety | 3 | 2
Depressed mood | 2 | 0
Depression | 2 | 0
Diplopia | 2 | 0
Hypersomnia | 2 | 0
Insomnia | 2 | 0
Irritability | 2 | 0
Nervousness | 2 | 0
Somnolence | 2 | 0

Primary Generalized Tonic-Clonic Seizures

Although the pattern of adverse reactions in this study seems somewhat different from that seen in patients with partial-onset seizures, this is likely due to the much smaller number of patients in this study compared to partial seizure studies. The adverse reaction pattern for patients with primary generalized tonic-clonic (PGTC) seizures is expected to be essentially the same as for patients with partial seizures.

In the controlled clinical study that included patients 4 years of age and older with PGTC seizures [see Clinical Studies (14.3)] , the most common adverse reaction in patients receiving KEPPRA in combination with other AEDs, for events with rates greater than placebo, was nasopharyngitis.

Table 9 lists adverse reactions that occurred in at least 5% of idiopathic generalized epilepsy patients experiencing PGTC seizures treated with KEPPRA and were numerically more common than in patients treated with placebo. In this study, either KEPPRA or placebo was added to concurrent AED therapy.

Table 9: Adverse Reactions in a Placebo-Controlled, Adjunctive Study in Patients 4 Years of Age and Older with PGTC Seizures
 | KEPPRA (N=79) % | Placebo (N=84) %
Nasopharyngitis | 14 | 5
Fatigue | 10 | 8
Diarrhea | 8 | 7
Irritability | 6 | 2
Mood swings | 5 | 1

In the placebo-controlled study, 5% of patients receiving KEPPRA and 8% receiving placebo either discontinued or had a dose reduction during the treatment period as a result of an adverse reaction.

This study was too small to adequately characterize the adverse reactions that could be expected to result in discontinuation of treatment in this population. It is expected that the adverse reactions that would lead to discontinuation in this population would be similar to those resulting in discontinuation in other epilepsy trials (see tables 4and 8).

In addition, the following adverse reactions were seen in other controlled adult studies of KEPPRA: balance disorder, disturbance in attention, eczema, memory impairment, myalgia, and blurred vision.

Comparison of Gender, Age and Race

The overall adverse reaction profile of KEPPRA was similar between females and males. There are insufficient data to support a statement regarding the distribution of adverse reactions by age and race.

6.2 Postmarketing Experience

The following adverse reactions have been identified during postapproval use of KEPPRA. Because these reactions are reported voluntarily from a population of uncertain size, it is not always possible to reliably estimate their frequency or establish a causal relationship to drug exposure.

The following adverse reactions have been reported in patients receiving marketed KEPPRA worldwide. The listing is alphabetized: abnormal liver function test, acute kidney injury, anaphylaxis, angioedema, agranulocytosis, choreoathetosis, drug reaction with eosinophilia and systemic symptoms (DRESS), dyskinesia, erythema multiforme, hepatic failure, hepatitis, hyponatremia, muscular weakness, obsessive-compulsive disorders (OCD), pancreatitis, pancytopenia (with bone marrow suppression identified in some of these cases), panic attack, thrombocytopenia, weight loss, and worsening of seizures including in patients with SCN8A mutations. Alopecia has been reported with KEPPRA use; recovery was observed in majority of cases where KEPPRA was discontinued.

8 USE IN SPECIFIC POPULATIONS

8.1 Pregnancy

Pregnancy Exposure Registry

There is a pregnancy exposure registry that monitors pregnancy outcomes in women exposed to antiepileptic drugs (AEDs), including KEPPRA, during pregnancy. Encourage women who are taking KEPPRA during pregnancy to enroll in the North American Antiepileptic Drug (NAAED) pregnancy registry by calling 1-888-233-2334 or visiting http://www.aedpregnancyregistry.org/.

Risk Summary

Prolonged experience with KEPPRA in pregnant women has not identified a drug-associated risk of major birth defects or miscarriage, based on published literature, which includes data from pregnancy registries and reflects experience over two decades [see Human Data] . In animal studies, levetiracetam produced developmental toxicity (increased embryofetal and offspring mortality, increased incidences of fetal structural abnormalities, decreased embryofetal and offspring growth, neurobehavioral alterations in offspring) at doses similar to human therapeutic doses [see Animal Data] .

In the U.S. general population, the estimated background risk of major birth defects and miscarriage in clinically recognized pregnancies is 2-4% and 15-20%, respectively. The background risk of major birth defects and miscarriage for the indicated population is unknown.

Clinical Considerations

Levetiracetam blood levels may decrease during pregnancy [see Warnings and Precautions (5.11)] .

Physiological changes during pregnancy may affect levetiracetam concentration. Decrease in levetiracetam plasma concentrations has been observed during pregnancy. This decrease is more pronounced during the third trimester. Dose adjustments may be necessary to maintain clinical response.

Data

Human Data

While available studies cannot definitively establish the absence of risk, data from the published literature and pregnancy registries have not established an association with levetiracetam use during pregnancy and major birth defects or miscarriage.

Animal Data

When levetiracetam (0, 400, 1200, or 3600 mg/kg/day) was administered orally to pregnant rats during the period of organogenesis, reduced fetal weights and increased incidence of fetal skeletal variations were observed at the highest dose tested. There was no evidence of maternal toxicity. The no-effect dose for adverse effects on embryofetal developmental in rats (1200 mg/kg/day) is approximately 4 times the maximum recommended human dose (MRHD) of 3000 mg on a body surface area (mg/m^2) basis.

Oral administration of levetiracetam (0, 200, 600, or 1800 mg/kg/day) to pregnant rabbits during the period of organogenesis resulted in increased embryofetal mortality and incidence of fetal skeletal variations at the mid and high dose and decreased fetal weights and increased incidence of fetal malformations at the high dose, which was associated with maternal toxicity. The no-effect dose for adverse effects on embryofetal development in rabbits (200 mg/kg/day) is approximately equivalent to the MRHD on a mg/m^2basis.

Oral administration of levetiracetam (0, 70, 350, or 1800 mg/kg/day) to female rats throughout pregnancy and lactation led to an increased incidence of fetal skeletal variations, reduced fetal body weight, and decreased growth in offspring at the mid and high doses and increased pup mortality and neurobehavioral alterations in offspring at the highest dose tested. There was no evidence of maternal toxicity. The no-effect dose for adverse effects on pre- and postnatal development in rats (70 mg/kg/day) is less than the MRHD on a mg/m^2basis.

Oral administration of levetiracetam to rats during the latter part of gestation and throughout lactation produced no adverse developmental or maternal effects at doses of up to 1800 mg/kg/day (6 times the MRHD on a mg/m^2basis).

8.2 Lactation

Risk Summary

Levetiracetam is excreted in human milk. There are no data on the effects of KEPPRA on the breastfed infant, or the effects on milk production.

The developmental and health benefits of breastfeeding should be considered along with the mother's clinical need for KEPPRA and any potential adverse effects on the breastfed infant from KEPPRA or from the underlying maternal condition.

8.4 Pediatric Use

The safety and effectiveness of KEPPRA for the treatment of partial-onset seizures in patients 1 month to 16 years of age have been established [see Clinical Pharmacology (12.3)and Clinical Studies (14.1)] . The dosing recommendation in these pediatric patients varies according to age group and is weight-based [see Dosage and Administration (2.2)] .

The safety and effectiveness of KEPPRA as adjunctive therapy for the treatment of myoclonic seizures in adolescents 12 years of age and older with juvenile myoclonic epilepsy have been established [see Clinical Studies (14.2)] .

The safety and effectiveness of KEPPRA as adjunctive therapy for the treatment of primary generalized tonic-clonic seizures in pediatric patients 6 years of age and older with idiopathic generalized epilepsy have been established [see Clinical Studies (14.3)] .

Safety and effectiveness for the treatment of partial-onset seizures in pediatric patients below the age of 1 month; adjunctive therapy for the treatment of myoclonic seizures in pediatric patients below the age of 12 years; and adjunctive therapy for the treatment of primary generalized tonic-clonic seizures in pediatric patients below the age of 6 years have not been established.

A 3-month, randomized, double-blind, placebo-controlled study was performed to assess the neurocognitive and behavioral effects of KEPPRA as adjunctive therapy in 98 (KEPPRA N=64, placebo N=34) pediatric patients, ages 4 to 16 years old, with partial seizures that were inadequately controlled. The target dose was 60 mg/kg/day. Neurocognitive effects were measured by the Leiter-R Attention and Memory (AM) Battery, which measures various aspects of a child's memory and attention. Although no substantive differences were observed between the placebo and drug treated groups in the median change from baseline in this battery, the study was not adequate to assess formal statistical non-inferiority of the drug and placebo. The Achenbach Child Behavior Checklist (CBCL/6-18), a standardized validated tool used to assess a child's competencies and behavioral/emotional problems, was also assessed in this study. An analysis of the CBCL/6-18 indicated on average a worsening in KEPPRA-treated patients in aggressive behavior, one of the eight syndrome scores [see Warnings and Precautions (5.1)] .

Juvenile Animal Toxicity Data

Studies of levetiracetam in juvenile rats (dosed on postnatal days 4 through 52) and dogs (dosed from postnatal weeks 3 through 7) at doses of up to 1800 mg/kg/day (approximately 7 and 24 times, respectively, the maximum recommended pediatric dose of 60 mg/kg/day on a mg/m^2basis) did not demonstrate adverse effects on postnatal development.

8.5 Geriatric Use

There were 347 subjects in clinical studies of KEPPRA that were 65 and over. No overall differences in safety were observed between these subjects and younger subjects. There were insufficient numbers of elderly subjects in controlled trials of epilepsy to adequately assess the effectiveness of KEPPRA in these patients.

Levetiracetam is known to be substantially excreted by the kidney, and the risk of adverse reactions to this drug may be greater in patients with impaired renal function. Because elderly patients are more likely to have decreased renal function, care should be taken in dose selection, and it may be useful to monitor renal function [see Clinical Pharmacology (12.3)] .

8.6 Renal Impairment

Clearance of levetiracetam is decreased in patients with renal impairment and is correlated with creatinine clearance [see Clinical Pharmacology (12.3)] . Dose adjustment is recommended for patients with impaired renal function and supplemental doses should be given to patients after dialysis [see Dosage and Administration (2.5)] .

10 OVERDOSAGE

10.1 Signs, Symptoms and Laboratory Findings of Acute Overdosage in Humans

The highest known dose of KEPPRA received in the clinical development program was 6000 mg/day. Other than drowsiness, there were no adverse reactions in the few known cases of overdose in clinical trials. Cases of somnolence, agitation, aggression, depressed level of consciousness, respiratory depression and coma were observed with KEPPRA overdoses in postmarketing use.

10.2 Management of Overdose

There is no specific antidote for overdose with KEPPRA. If indicated, elimination of unabsorbed drug should be attempted by emesis or gastric lavage; usual precautions should be observed to maintain airway. General supportive care of the patient is indicated including monitoring of vital signs and observation of the patient's clinical status. A Certified Poison Control Center should be contacted for up to date information on the management of overdose with KEPPRA.

10.3 Hemodialysis

Standard hemodialysis procedures result in significant clearance of levetiracetam (approximately 50% in 4 hours) and should be considered in cases of overdose. Although hemodialysis has not been performed in the few known cases of overdose, it may be indicated by the patient's clinical state or in patients with significant renal impairment.

11 DESCRIPTION

KEPPRA is an antiepileptic drug available as 250 mg (blue), 500 mg (yellow), 750 mg (orange), and 1000 mg (white) tablets and as a clear, colorless, grape-flavored liquid (100 mg/mL) for oral administration.

The chemical name of levetiracetam, a single enantiomer, is (-)-(S)-α-ethyl-2-oxo-1-pyrrolidine acetamide, its molecular formula is C8H14N2O2 and its molecular weight is 170.21. Levetiracetam is chemically unrelated to existing antiepileptic drugs (AEDs). It has the following structural formula:

Levetiracetam is a white to off-white crystalline powder with a faint odor and a bitter taste. It is very soluble in water (104.0 g/100 mL). It is freely soluble in chloroform (65.3 g/100 mL) and in methanol (53.6 g/100 mL), soluble in ethanol (16.5 g/100 mL), sparingly soluble in acetonitrile (5.7 g/100 mL) and practically insoluble in n-hexane. (Solubility limits are expressed as g/100 mL solvent.)

KEPPRA tablets contain the labeled amount of levetiracetam. Inactive ingredients: colloidal silicon dioxide, croscarmellose sodium, magnesium stearate, polyethylene glycol 3350, polyethylene glycol 6000, polyvinyl alcohol, talc, titanium dioxide, and additional agents listed below:

250 mg tablets: FD&C Blue #2/indigo carmine aluminum lake
500 mg tablets: iron oxide yellow
750 mg tablets: FD&C yellow #6/sunset yellow FCF aluminum lake, iron oxide red

KEPPRA oral solution contains 100 mg of levetiracetam per mL. Inactive ingredients: ammonium glycyrrhizinate, citric acid monohydrate, glycerin, maltitol solution, methylparaben, potassium acesulfame, propylparaben, purified water, sodium citrate dihydrate and natural and artificial flavor.

12 CLINICAL PHARMACOLOGY

12.1 Mechanism of Action

The precise mechanism(s) by which levetiracetam exerts its antiepileptic effect is unknown.

A saturable and stereoselective neuronal binding site in rat brain tissue has been described for levetiracetam. Experimental data indicate that this binding site is the synaptic vesicle protein SV2A, thought to be involved in the regulation of vesicle exocytosis. Although the molecular significance of levetiracetam binding to SV2A is not understood, levetiracetam and related analogs showed a rank order of affinity for SV2A which correlated with the potency of their antiseizure activity in audiogenic seizure-prone mice. These findings suggest that the interaction of levetiracetam with the SV2A protein may contribute to the antiepileptic mechanism of action of the drug.

12.2 Pharmacodynamics

Effects on QTc Interval

The effect of KEPPRA on QTc prolongation was evaluated in a randomized, double-blind, positive-controlled (moxifloxacin 400 mg) and placebo-controlled crossover study of KEPPRA (1000 mg or 5000 mg) in 52 healthy subjects. The upper bound of the 90% confidence interval for the largest placebo-adjusted, baseline-corrected QTc was below 10 milliseconds. Therefore, there was no evidence of significant QTc prolongation in this study.

12.3 Pharmacokinetics

The pharmacokinetics of levetiracetam are similar when used as monotherapy or as adjunctive therapy for the treatment of partial-onset seizures.

Absorption and Distribution

Absorption of levetiracetam is rapid, with peak plasma concentrations occurring in about an hour following oral administration in fasted subjects. The oral bioavailability of levetiracetam tablets is 100% and the tablets and oral solution are bioequivalent in rate and extent of absorption. Food does not affect the extent of absorption of levetiracetam but it decreases Cmaxby 20% and delays Tmaxby 1.5 hours. The pharmacokinetics of levetiracetam are linear over the dose range of 500-5000 mg. Steady state is achieved after 2 days of multiple twice-daily dosing. Levetiracetam and its major metabolite are less than 10% bound to plasma proteins; clinically significant interactions with other drugs through competition for protein binding sites are therefore unlikely.

Metabolism

Levetiracetam is not extensively metabolized in humans. The major metabolic pathway is the enzymatic hydrolysis of the acetamide group, which produces the carboxylic acid metabolite, ucb L057 (24% of dose) and is not dependent on any liver cytochrome P450 isoenzymes. The major metabolite is inactive in animal seizure models. Two minor metabolites were identified as the product of hydroxylation of the 2-oxo-pyrrolidine ring (2% of dose) and opening of the 2-oxo-pyrrolidine ring in position 5 (1% of dose). There is no enantiomeric interconversion of levetiracetam or its major metabolite.

Elimination

Levetiracetam plasma half-life in adults is 7 ± 1 hour and is unaffected by either dose or repeated administration. Levetiracetam is eliminated from the systemic circulation by renal excretion as unchanged drug which represents 66% of administered dose. The total body clearance is 0.96 mL/min/kg and the renal clearance is 0.6 mL/min/kg. The mechanism of excretion is glomerular filtration with subsequent partial tubular reabsorption. The metabolite ucb L057 is excreted by glomerular filtration and active tubular secretion with a renal clearance of 4 mL/min/kg. Levetiracetam elimination is correlated to creatinine clearance. Levetiracetam clearance is reduced in patients with renal impairment [see Use in Specific Populations (8.6)and Dosage and Administration (2.5)] .

Specific Populations

Elderly

Pharmacokinetics of levetiracetam were evaluated in 16 elderly subjects (age 61-88 years) with creatinine clearance ranging from 30 to 74 mL/min. Following oral administration of twice-daily dosing for 10 days, total body clearance decreased by 38% and the half-life was 2.5 hours longer in the elderly compared to healthy adults. This is most likely due to the decrease in renal function in these subjects.

Pediatric Patients

Pharmacokinetics of levetiracetam were evaluated in 24 pediatric patients (age 6-12 years) after single dose (20 mg/kg). The body weight adjusted apparent clearance of levetiracetam was approximately 40% higher than in adults.

A repeat dose pharmacokinetic study was conducted in pediatric patients (age 4-12 years) at doses of 20 mg/kg/day, 40 mg/kg/day, and 60 mg/kg/day. The evaluation of the pharmacokinetic profile of levetiracetam and its metabolite (ucb L057) in 14 pediatric patients demonstrated rapid absorption of levetiracetam at all doses with a Tmaxof about 1 hour and a t1/2of 5 hours across the three dosing levels. The pharmacokinetics of levetiracetam in children was linear between 20 to 60 mg/kg/day. The potential interaction of levetiracetam with other AEDs was also evaluated in these patients. Levetiracetam had no significant effect on the plasma concentrations of carbamazepine, valproic acid, topiramate or lamotrigine. However, there was about a 22% increase of apparent clearance of levetiracetam when it was co-administered with an enzyme-inducing AED (e.g. carbamazepine).

Following single dose administration (20 mg/kg) of a 10% oral solution to children with epilepsy (1 month to < 4 years), levetiracetam was rapidly absorbed and peak plasma concentrations were observed approximately 1 hour after dosing. The pharmacokinetic results indicated that half-life was shorter (5.3 h) than for adults (7.2 h) and apparent clearance was faster (1.5 mL/min/kg) than for adults (0.96 mL/min/kg).

Population pharmacokinetic analysis showed that body weight was significantly correlated to the clearance of levetiracetam in pediatric patients; clearance increased with an increase in body weight.

Pediatric Patients with Obesity

A population PK analysis of levetiracetam was conducted in 164 obese and non-obese pediatric patients 2 to <18 years of age with median (range) weight 39.2 (11.3-134) kg to evaluate the potential impact of obesity on plasma levetiracetam exposures. Obesity was defined as BMI ≥95th percentile for age and sex based on CDC 2000 growth chart recommendations. Simulations were conducted for obese and non-obese pediatric patients ages 4 to <16 years.

- When the recommended tablet dose is administered to pediatric patients weighing < 40 kg, obese pediatric patients have 27% higher median Cmax,ssand 19% higher median Cmin,sscompared to non-obese patients.
- When the recommended tablet dose is administered to pediatric patients weighing ≥ 40 kg, obese pediatric patients have 10-11% lower median Cmax,ssand 2% lower median Cmin,sscompared to non-obese patients.
- When the recommended oral solution dose is administered to pediatric patients across the full weight range, obese pediatric patients have 25% higher median Cmax,ssand 41% higher median Cmin,sscompared to non-obese pediatric patients.

However, differences in exposures between obese and non-obese pediatric patients are not expected to be clinically meaningful because the recommended dose titration at initiation of levetiracetam therapy would establish an appropriate dose for each individual patient.

Pregnancy

Levetiracetam levels may decrease during pregnancy [see Warnings and Precautions (5.11)and Use in Specific Populations (8.1)].

Gender

Levetiracetam Cmaxand AUC were 20% higher in women (N=11) compared to men (N=12). However, clearances adjusted for body weight were comparable.

Race

Formal pharmacokinetic studies of the effects of race have not been conducted. Cross-study comparisons involving Caucasians (N=12) and Asians (N=12), however, show that pharmacokinetics of levetiracetam were comparable between the two races. Because levetiracetam is primarily renally excreted and there are no important racial differences in creatinine clearance, pharmacokinetic differences due to race are not expected.

Renal Impairment

The disposition of levetiracetam was studied in adult subjects with varying degrees of renal function. Total body clearance of levetiracetam is reduced in patients with impaired renal function by 40% in the mild group (CLcr = 50-80 mL/min), 50% in the moderate group (CLcr = 30-50 mL/min) and 60% in the severe renal impairment group (CLcr <30 mL/min). Clearance of levetiracetam is correlated with creatinine clearance.

In anuric (end stage renal disease) patients, the total body clearance decreased 70% compared to normal subjects (CLcr >80 mL/min). Approximately 50% of the pool of levetiracetam in the body is removed during a standard 4- hour hemodialysis procedure [see Dosage and Administration (2.5)] .

Hepatic Impairment

In subjects with mild (Child-Pugh A) to moderate (Child-Pugh B) hepatic impairment, the pharmacokinetics of levetiracetam were unchanged. In patients with severe hepatic impairment (Child-Pugh C), total body clearance was 50% that of normal subjects, but decreased renal clearance accounted for most of the decrease. No dose adjustment is needed for patients with hepatic impairment.

Drug Interactions

In vitrodata on metabolic interactions indicate that levetiracetam is unlikely to produce, or be subject to, pharmacokinetic interactions. Levetiracetam and its major metabolite, at concentrations well above Cmaxlevels achieved within the therapeutic dose range, are neither inhibitors of, nor high affinity substrates for, human liver cytochrome P450 isoforms, epoxide hydrolase or UDP-glucuronidation enzymes. In addition, levetiracetam does not affect the in vitroglucuronidation of valproic acid.

Potential pharmacokinetic interactions of or with levetiracetam were assessed in clinical pharmacokinetic studies (phenytoin, valproate, warfarin, digoxin, oral contraceptive, probenecid) and through pharmacokinetic screening in the placebo-controlled clinical studies in epilepsy patients.

Phenytoin

KEPPRA (3000 mg daily) had no effect on the pharmacokinetic disposition of phenytoin in patients with refractory epilepsy. Pharmacokinetics of levetiracetam were also not affected by phenytoin.

Valproate

KEPPRA (1500 mg twice daily) did not alter the pharmacokinetics of valproate in healthy volunteers. Valproate 500 mg twice daily did not modify the rate or extent of levetiracetam absorption or its plasma clearance or urinary excretion. There also was no effect on exposure to and the excretion of the primary metabolite, ucb L057.

Other Antiepileptic Drugs

Potential drug interactions between KEPPRA and other AEDs (carbamazepine, gabapentin, lamotrigine, phenobarbital, phenytoin, primidone and valproate) were also assessed by evaluating the serum concentrations of levetiracetam and these AEDs during placebo-controlled clinical studies. These data indicate that levetiracetam does not influence the plasma concentration of other AEDs and that these AEDs do not influence the pharmacokinetics of levetiracetam.

Effect of AEDs in Pediatric Patients

There was about a 22% increase of apparent total body clearance of levetiracetam when it was co-administered with enzyme-inducing AEDs. Dose adjustment is not recommended. Levetiracetam had no effect on plasma concentrations of carbamazepine, valproate, topiramate, or lamotrigine.

Oral Contraceptives

KEPPRA (500 mg twice daily) did not influence the pharmacokinetics of an oral contraceptive containing 0.03 mg ethinyl estradiol and 0.15 mg levonorgestrel, or of the luteinizing hormone and progesterone levels, indicating that impairment of contraceptive efficacy is unlikely. Coadministration of this oral contraceptive did not influence the pharmacokinetics of levetiracetam.

Digoxin

KEPPRA (1000 mg twice daily) did not influence the pharmacokinetics and pharmacodynamics (ECG) of digoxin given as a 0.25 mg dose every day. Coadministration of digoxin did not influence the pharmacokinetics of levetiracetam.

Warfarin

KEPPRA (1000 mg twice daily) did not influence the pharmacokinetics of R and S warfarin. Prothrombin time was not affected by levetiracetam. Coadministration of warfarin did not affect the pharmacokinetics of levetiracetam.

Probenecid

Probenecid, a renal tubular secretion blocking agent, administered at a dose of 500 mg four times a day, did not change the pharmacokinetics of levetiracetam 1000 mg twice daily. Cssmaxof the metabolite, ucb L057, was approximately doubled in the presence of probenecid while the fraction of drug excreted unchanged in the urine remained the same. Renal clearance of ucb L057 in the presence of probenecid decreased 60%, probably related to competitive inhibition of tubular secretion of ucb L057. The effect of KEPPRA on probenecid was not studied.

13 NONCLINICAL TOXICOLOGY

13.1 Carcinogenesis, Mutagenesis, Impairment of Fertility

Carcinogenesis

Rats were dosed with levetiracetam in the diet for 104 weeks at doses of 50, 300, and 1800 mg/kg/day. Plasma exposure (AUC) at the highest dose was approximately 6 times that in humans at the maximum recommended daily human dose (MRHD) of 3000 mg. There was no evidence of carcinogenicity. In mice, oral administration of levetiracetam for 80 weeks (doses up to 960 mg/kg/day) or 2 years (doses up to 4000 mg/kg/day, lowered to 3000 mg/kg/day after 45 weeks due to intolerability) was not associated with an increase in tumors. The highest dose tested in mice for 2 years (3000 mg/kg/day) is approximately 5 times the MRHD on a body surface area (mg/m^2) basis.

Mutagenesis

Levetiracetam was negative in in vitro(Ames, chromosomal aberration in mammalian cells) and in vivo(mouse micronucleus) assays. The major human metabolite of levetiracetam (ucb L057) was negative in in vitro(Ames, mouse lymphoma) assays.

Impairment of Fertility

No adverse effects on male or female fertility or reproductive performance were observed in rats at oral doses up to 1800 mg/kg/day, which were associated with plasma exposures (AUC) up to approximately 6 times that in humans at the MRHD.

14 CLINICAL STUDIES

14.1 Partial-Onset Seizures

Effectiveness in Partial-Onset Seizures in Adults

The effectiveness of KEPPRA for the treatment of partial-onset seizures in adults was established in three multicenter, randomized, double-blind, placebo-controlled clinical studies in patients who had refractory partial-onset seizures with or without secondary generalization. The tablet formulation was used in all these studies. In these studies, 904 patients were randomized to placebo, 1000 mg, 2000 mg, or 3000 mg/day. Patients enrolled in Study 1 or Study 2 had refractory partial-onset seizures for at least two years and had taken two or more classical AEDs. Patients enrolled in Study 3 had refractory partial-onset seizures for at least 1 year and had taken one classical AED. At the time of the study, patients were taking a stable dose regimen of at least one and could take a maximum of two AEDs. During the baseline period, patients had to have experienced at least two partial- onset seizures during each 4-week period.

Study 1

Study 1 was a double-blind, placebo-controlled, parallel-group study conducted at 41 sites in the United States comparing KEPPRA 1000 mg/day (N=97), KEPPRA 3000 mg/day (N=101), and placebo (N=95) given in equally divided doses twice daily. After a prospective baseline period of 12 weeks, patients were randomized to one of the three treatment groups described above. The 18-week treatment period consisted of a 6-week titration period, followed by a 12-week fixed dose evaluation period, during which concomitant AED regimens were held constant. The primary measure of effectiveness was a between group comparison of the percent reduction in weekly partial seizure frequency relative to placebo over the entire randomized treatment period (titration + evaluation period). Secondary outcome variables included the responder rate (incidence of patients with ≥50% reduction from baseline in partial-onset seizure frequency). The results of the analysis of Study 1 are displayed in Table 10.

Table 10: Reduction in Mean Over Placebo in Weekly Frequency of Partial-Onset Seizures in Study 1
 | Placebo (N=95) | KEPPRA 1000 mg/day (N=97) | KEPPRA 3000 mg/day (N=101)
Percent reduction in partial seizure frequency over placebo | – | 26.1% [statistically significant versus placebo] | 30.1%

The percentage of patients (y-axis) who achieved ≥50% reduction in weekly seizure rates from baseline in partial-onset seizure frequency over the entire randomized treatment period (titration + evaluation period) within the three treatment groups (x-axis) is presented in Figure 1.

Figure 1: Responder Rate (≥50% Reduction from Baseline) in Study 1

*statistically significant versus placebo

Study 2

Study 2 was a double-blind, placebo-controlled, crossover study conducted at 62 centers in Europe comparing KEPPRA 1000 mg/day (N=106), KEPPRA 2000 mg/day (N=105), and placebo (N=111) given in equally divided doses twice daily.

The first period of the study (Period A) was designed to be analyzed as a parallel-group study. After a prospective baseline period of up to 12 weeks, patients were randomized to one of the three treatment groups described above. The 16-week treatment period consisted of the 4-week titration period followed by a 12-week fixed dose evaluation period, during which concomitant AED regimens were held constant. The primary measure of effectiveness was a between group comparison of the percent reduction in weekly partial seizure frequency relative to placebo over the entire randomized treatment period (titration + evaluation period). Secondary outcome variables included the responder rate (incidence of patients with ≥50% reduction from baseline in partial-onset seizure frequency). The results of the analysis of Period A are displayed in Table 11.

Table 11: Reduction in Mean Over Placebo in Weekly Frequency of Partial-Onset Seizures in Study 2: Period A
 | Placebo (N=111) | KEPPRA 1000 mg/day (N=106) | KEPPRA 2000 mg/day (N=105)
Percent reduction in partial seizure frequency over placebo | – | 17.1% [statistically significant versus placebo] | 21.4%

The percentage of patients (y-axis) who achieved ≥50% reduction in weekly seizure rates from baseline in partial-onset seizure frequency over the entire randomized treatment period (titration + evaluation period) within the three treatment groups (x-axis) is presented in Figure 2.

Figure 2: Responder Rate (≥50% Reduction from Baseline) in Study 2: Period A

*statistically significant versus placebo

The comparison of KEPPRA 2000 mg/day to KEPPRA 1000 mg/day for responder rate was statistically significant (P=0.02). Analysis of the trial as a cross-over yielded similar results.

Study 3

Study 3 was a double-blind, placebo-controlled, parallel-group study conducted at 47 centers in Europe comparing KEPPRA 3000 mg/day (N=180) and placebo (N=104) in patients with refractory partial-onset seizures, with or without secondary generalization, receiving only one concomitant AED. Study drug was given in two divided doses. After a prospective baseline period of 12 weeks, patients were randomized to one of two treatment groups described above. The 16-week treatment period consisted of a 4-week titration period, followed by a 12-week fixed dose evaluation period, during which concomitant AED doses were held constant. The primary measure of effectiveness was a between group comparison of the percent reduction in weekly seizure frequency relative to placebo over the entire randomized treatment period (titration + evaluation period). Secondary outcome variables included the responder rate (incidence of patients with ≥50% reduction from baseline in partial-onset seizure frequency). Table 12 displays the results of the analysis of Study 3.

Table 12: Reduction in Mean Over Placebo in Weekly Frequency of Partial-Onset Seizures in Study 3
 | Placebo (N=104) | KEPPRA 3000 mg/day (N=180)
Percent reduction in partial seizure frequency over placebo | – | 23.0% [statistically significant versus placebo]

The percentage of patients (y-axis) who achieved ≥50% reduction in weekly seizure rates from baseline in partial-onset seizure frequency over the entire randomized treatment period (titration + evaluation period) within the two treatment groups (x-axis) is presented in Figure 3.

Figure 3: Responder Rate (≥50% Reduction from Baseline) in Study 3

*statistically significant versus placebo

Effectiveness in Partial-Onset Seizures in Pediatric Patients 4 to 16 Years of Age

The effectiveness of KEPPRA for the treatment of partial-onset seizures in pediatric patients was established in one multicenter, randomized double-blind, placebo-controlled study (Study 4), conducted at 60 sites in North America, in pediatric patients 4 to 16 years of age with partial seizures uncontrolled by standard antiepileptic drugs (AEDs). Eligible patients on a stable dose of 1-2 AEDs, who still experienced at least 4 partial- onset seizures during the 4 weeks prior to screening, as well as at least 4 partial-onset seizures in each of the two 4-week baseline periods, were randomized to receive either KEPPRA or placebo. The enrolled population included 198 patients (KEPPRA N=101, placebo N=97) with refractory partial-onset seizures, whether or not secondarily generalized. The study consisted of an 8-week baseline period and 4-week titration period followed by a 10-week evaluation period. Dosing was initiated at a dose of 20 mg/kg/day in two divided doses. During the treatment period, KEPPRA doses were adjusted in 20 mg/kg/day increments, at 2-week intervals to the target dose of 60 mg/kg/day. The primary measure of effectiveness was a between group comparison of the percent reduction in weekly partial seizure frequency relative to placebo over the entire 14-week randomized treatment period (titration + evaluation period). Secondary outcome variables included the responder rate (incidence of patients with ≥ 50% reduction from baseline in partial-onset seizure frequency per week). Table 13 displays the results of this study.

Table 13: Reduction in Mean Over Placebo in Weekly Frequency of Partial-Onset Seizures in Study 4
 | Placebo (N=97) | KEPPRA (N=101)
Percent reduction in partial seizure frequency over placebo | - | 26.8% [statistically significant versus placebo]

The percentage of patients (y-axis) who achieved ≥ 50% reduction in weekly seizure rates from baseline in partial-onset seizure frequency over the entire randomized treatment period (titration + evaluation period) within the two treatment groups (x-axis) is presented in Figure 4.

Figure 4: Responder Rate (≥ 50% Reduction from Baseline) in Study 4

*statistically significant versus placebo

Effectiveness in Partial-Onset Seizures in Pediatric Patients 1 Month to <4 Years of Age

The effectiveness of KEPPRA for the treatment of partial-onset seizures in pediatric patients was established in one multicenter, randomized double-blind, placebo-controlled study (Study 5), conducted at 62 sites in North America, South America, and Europe in pediatric patients 1 month to less than 4 years of age with partial seizures, uncontrolled by standard epileptic drugs (AEDs). Eligible patients on a stable dose of 1-2 AEDs, who experienced at least 2 partial -onset seizures during the 48-hour baseline video EEG were randomized to receive either KEPPRA or placebo. The enrolled population included 116 patients (KEPPRA N=60, placebo N=56) with refractory partial-onset seizures, whether or not secondarily generalized. Randomization was stratified by age range as follows: 1 month to less than 6 months of age (N=4 treated with KEPPRA), 6 months to less than 1 year of age (N=8 treated with KEPPRA), 1 year to less than 2 years of age (N=20 treated with KEPPRA), and 2 years to less than 4 years of age (N=28 treated with KEPPRA). The study consisted of a 5-day evaluation period which included a 1-day titration period followed by a 4-day maintenance period. KEPPRA dosing was determined by age and weight as follows: children 1 month to less than 6 months old were randomized to a target dose of 40 mg/kg/day, and children 6 months to less than 4 years old were randomized to a target dose of 50 mg/kg/day. The primary measure of effectiveness was the responder rate (percent of patients with ≥ 50% reduction from baseline in average daily partial-onset seizure frequency) assessed by a blinded central reader using a 48-hour video EEG performed during the last two days of the 4-day maintenance period. A total of 109 patients were included in the efficacy analysis. A statistically significant difference between KEPPRA and placebo was observed (see Figure 5). The treatment effect associated with KEPPRA was consistent across age groups.

Figure 5: Responder Rate for All Patients Ages 1 Month to < 4 Years (≥ 50% Reduction from Baseline) in Study 5

*statistically significant versus placebo

14.2 Myoclonic Seizures in Patients with Juvenile Myoclonic Epilepsy

The effectiveness of KEPPRA as adjunctive therapy in patients 12 years of age and older with juvenile myoclonic epilepsy (JME) experiencing myoclonic seizures was established in one multicenter, randomized, double-blind, placebo-controlled study (Study 6), conducted at 37 sites in 14 countries. Eligible patients on a stable dose of 1 antiepileptic drug (AED) experiencing one or more myoclonic seizures per day for at least 8 days during the prospective 8-week baseline period were randomized to either KEPPRA or placebo (KEPPRA N=60, placebo N=60). Patients were titrated over 4 weeks to a target dose of 3000 mg/day and treated at a stable dose of 3000 mg/day over 12 weeks (evaluation period). Study drug was given in 2 divided doses.

The primary measure of effectiveness was the proportion of patients with at least 50% reduction in the number of days per week with one or more myoclonic seizures during the treatment period (titration + evaluation periods) as compared to baseline. Of the 120 patients enrolled, 113 had a diagnosis of confirmed or suspected JME. Table 14 displays the results for the 113 patients with JME in this study.

Table 14: Responder Rate (≥50% Reduction from Baseline) in Myoclonic Seizure Days per Week for Patients with JME in Study 6
 | Placebo (N=59) | KEPPRA (N=54)
Percentage of responders | 23.7% | 60.4% [statistically significant versus placebo]

14.3 Primary Generalized Tonic-Clonic Seizures

The effectiveness of KEPPRA as adjunctive therapy in patients 6 years of age and older with idiopathic generalized epilepsy experiencing primary generalized tonic-clonic (PGTC) seizures was established in one multicenter, randomized, double-blind, placebo-controlled study (Study 7), conducted at 50 sites in 8 countries. Eligible patients on a stable dose of 1 or 2 antiepileptic drugs (AEDs) experiencing at least 3 PGTC seizures during the 8-week combined baseline period (at least one PGTC seizure during the 4 weeks prior to the prospective baseline period and at least one PGTC seizure during the 4-week prospective baseline period) were randomized to either KEPPRA or placebo. The 8-week combined baseline period is referred to as "baseline" in the remainder of this section. Patients were titrated over 4 weeks to a target dose of 3000 mg/day for adults or a pediatric target dose of 60 mg/kg/day and treated at a stable dose of 3000 mg/day (or 60 mg/kg/day for children) over 20 weeks (evaluation period). Study drug was given in 2 equally divided doses per day. The primary measure of effectiveness was the percent reduction from baseline in weekly PGTC seizure frequency for KEPPRA and placebo treatment groups over the treatment period (titration + evaluation periods). The population included 164 patients (KEPPRA N=80, placebo N=84) with idiopathic generalized epilepsy (predominately juvenile myoclonic epilepsy, juvenile absence epilepsy, childhood absence epilepsy, or epilepsy with Grand Mal seizures on awakening) experiencing primary generalized tonic-clonic seizures. Each of these syndromes of idiopathic generalized epilepsy was well represented in this patient population.

There was a statistically significant decrease from baseline in PGTC frequency in the KEPPRA-treated patients compared to the placebo-treated patients.

Table 15: Median Percent Reduction from Baseline in PGTC Seizure Frequency per Week in Study 7
 | Placebo (N=84) | KEPPRA (N=78)
Percent reduction in PGTC seizure frequency | 44.6% | 77.6% [statistically significant versus placebo]

The percentage of patients (y-axis) who achieved ≥50% reduction in weekly seizure rates from baseline in PGTC seizure frequency over the entire randomized treatment period (titration + evaluation period) within the two treatment groups (x-axis) is presented in Figure 6.

Figure 6: Responder Rate (≥50% Reduction from Baseline) in PGTC Seizure Frequency per Week in Study 7

*statistically significant versus placebo

16 HOW SUPPLIED/STORAGE AND HANDLING

16.1 How Supplied

KEPPRA Tablets

- 250 mg: blue, oblong-shaped, scored, film-coated tablets debossed with "ucb 250" on one side. They are supplied in white HDPE bottles containing 120 tablets (NDC 50474-594-40).
- 500 mg: yellow, oblong-shaped, scored, film-coated tablets debossed with "ucb 500" on one side. They are supplied in white HDPE bottles containing 120 tablets (NDC 50474-595-40).
- 750 mg: orange, oblong-shaped, scored, film-coated tablets debossed with "ucb 750" on one side. They are supplied in white HDPE bottles containing 120 tablets (NDC 50474-596-40).
- 1000 mg: white, oblong-shaped, scored, film-coated tablets debossed with "ucb 1000" on one side. They are supplied in white HDPE bottles containing 60 tablets (NDC 50474-597-66).

KEPPRA Oral Solution

- 100 mg/mL: a clear, colorless, grape-flavored liquid. It is supplied in 16 fl. oz. white HDPE bottles (NDC 50474-001-48).

16.2 Storage

Store at 25°C (77°F); excursions permitted to 15°C to 30°C (59°F to 86°F) [see USP Controlled Room Temperature].

17 PATIENT COUNSELING INFORMATION

Advise the patient to read the FDA-approved patient labeling (Medication Guide). The Medication Guide accompanies the product and can also be accessed on www.keppra.com or by calling 1-844-599-2273.

Psychiatric Reactions and Changes in Behavior

Advise patients that KEPPRA may cause changes in behavior (e.g. aggression, agitation, anger, anxiety, apathy, depression, hostility, and irritability) and psychotic symptoms [see Warnings and Precautions (5.1)] .

Suicidal Behavior and Ideation

Counsel patients, their caregivers, and/or families that antiepileptic drugs (AEDs), including KEPPRA, may increase the risk of suicidal thoughts and behavior and advise patients to be alert for the emergence or worsening of symptoms of depression; unusual changes in mood or behavior; or suicidal thoughts, behavior, or thoughts about self-harm. Advise patients, their caregivers, and/or families to immediately report behaviors of concern to a healthcare provider [see Warnings and Precautions (5.2)] .

Effects on Driving or Operating Machinery

Inform patients that KEPPRA may cause dizziness and somnolence. Inform patients not to drive or operate machinery until they have gained sufficient experience on KEPPRA to gauge whether it adversely affects their ability to drive or operate machinery [see Warnings and Precautions (5.3)] .

Anaphylaxis and Angioedema

Advise patients to discontinue KEPPRA and seek medical care if they develop signs and symptoms of anaphylaxis or angioedema [see Warnings and Precautions (5.4)].

Dermatological Adverse Reactions

Advise patients that serious dermatological adverse reactions have occurred in patients treated with KEPPRA and instruct them to call their physician immediately if a rash develops [see Warnings and Precautions (5.5)] .

DRESS/Multiorgan Hypersensitivity

Instruct patients and caregivers that a fever or rash associated with signs of other organ system involvement (e.g., lymphadenopathy, hepatic dysfunction) may be drug-related and should be reported to their healthcare provider immediately. KEPPRA should be discontinued immediately if a serious hypersensitivity reaction is suspected [see Warnings and Precautions (5.6)].

Withdrawal of KEPPRA

Advise patients and caregivers not to discontinue use of KEPPRA without consulting with their healthcare provider. KEPPRA should normally be gradually withdrawn to reduce the potential of increased seizure frequency and status epilepticus [see Warnings and Precautions (5.8)].

Pregnancy

Advise patients to notify their healthcare provider if they become pregnant or intend to become pregnant during KEPPRA therapy. Encourage patients to enroll in the North American Antiepileptic Drug (NAAED) pregnancy registry if they become pregnant [see Use in Specific Populations (8.1)] .

KEPPRA Tablets and KEPPRA Oral Solution manufactured for
UCB, Inc.
Smyrna, GA 30080

KEPPRA is a registered trademark of the UCB Group of companies
© 2024, UCB, Inc., Smyrna, GA 30080
All rights reserved.

MEDICATION GUIDE
KEPPRA®(KEPP-ruh)(levetiracetam)
tablets, for oral use, and oral solution

Read this Medication Guide before you start taking KEPPRA and each time you get a refill. There may be new information. This information does not take the place of talking to your healthcare provider about your medical condition or treatment.

What is the most important information I should know about KEPPRA?
Like other antiepileptic drugs, KEPPRA may cause suicidal thoughts or actions in a very small number of people, about 1 in 500 people taking it.
Call a healthcare provider right away if you have any of these symptoms, especially if they are new, worse, or worry you:

- thoughts about suicide or dying
- attempts to commit suicide
- new or worse depression
- new or worse anxiety
- feeling agitated or restless
- panic attacks
- trouble sleeping (insomnia)
- new or worse irritability
- acting aggressive, being angry, or violent
- acting on dangerous impulses
- an extreme increase in activity and talking (mania)
- other unusual changes in behavior or mood

Do not stop KEPPRA without first talking to a healthcare provider.

- Stopping KEPPRA suddenly can cause serious problems. Stopping a seizure medicine suddenly can cause seizures that will not stop (status epilepticus).
- Suicidal thoughts or actions can be caused by things other than medicines. If you have suicidal thoughts or actions, your healthcare provider may check for other causes.

How can I watch for early symptoms of suicidal thoughts and actions?

- Pay attention to any changes, especially sudden changes, in mood, behaviors, thoughts, or feelings.
- Keep all follow-up visits with your healthcare provider as scheduled.

Call your healthcare provider between visits as needed, especially if you are worried about symptoms

What is KEPPRA?
KEPPRA is a prescription medicine taken by mouth that is used to treat partial-onset seizures in people 1 month of age and older.
KEPPRA is a prescription medicine taken by mouth that is used with other medicines to treat:

- myoclonic seizures in people 12 years of age and older with juvenile myoclonic epilepsy.
- primary generalized tonic-clonic seizures in people 6 years of age and older with certain types of generalized epilepsy.

It is not known if KEPPRA is safe or effective in children under:

- 1 month of age to treat partial-onset seizures
- 12 years of age to treat myoclonic seizures
- 6 years of age to treat primary generalized tonic-clonic seizures

Before taking your medicine, make sure you have received the correct medicine. Compare the name above with the name on your bottle and the appearance of your medicine with the description of KEPPRA provided below. Tell your pharmacist immediately if you think you have been given the wrong medicine.

Who should not take KEPPRA?
Do not take KEPPRA if you are allergic to levetiracetam.

What should I tell my healthcare provider before starting KEPPRA?
Before taking KEPPRA, tell your healthcare provider about all of your medical conditions, including if you:

- have or have had depression, mood problems or suicidal thoughts or behavior.
- have kidney problems.
- are pregnant or planning to become pregnant. It is not known if KEPPRA will harm your unborn baby. You and your healthcare provider will have to decide if you should take KEPPRA while you are pregnant. If you become pregnant while taking KEPPRA, talk to your healthcare provider about registering with the North American Antiepileptic Drug Pregnancy Registry. You can enroll in this registry by calling 1-888-233-2334 or go to http://www.aedpregnancyregistry.org. The purpose of this registry is to collect information about the safety of KEPPRA and other antiepileptic medicine during pregnancy.
- are breastfeeding or plan to breastfeed. KEPPRA can pass into your breast milk. It is not known if the KEPPRA that passes into your breast milk can harm your baby. Talk to your doctor about the best way to feed your baby while you receive KEPPRA.

Tell your healthcare provider about all the medicines you take, including prescription and over-the counter medicines, vitamins, and herbal supplements. Do not start a new medicine without first talking with your healthcare provider.
Know the medicines you take. Keep a list of them to show your healthcare provider and pharmacist each time you get a new medicine.

How should I take KEPPRA?

- Take KEPPRA exactly as your healthcare provider tells you to take it.
- Your healthcare provider will tell you how much KEPPRA to take and when to take it. KEPPRA is usually taken 2 times each day.
- Your healthcare provider may change your dose. Do notchange your dose without talking to your healthcare provider.
- Take KEPPRA with or without food.
- Swallow the tablets whole. Do notchew or crush tablets. Ask your healthcare provider for KEPPRA oral solution if you cannot swallow tablets.
- If your healthcare provider has prescribed KEPPRA oral solution, be sure to ask your pharmacist for a medicine dropper or medicine cup to help you measure the correct amount of KEPPRA oral solution. Do not use a household teaspoon. Ask your pharmacist for instructions on how to use the measuring device the right way.
- If you take too much KEPPRA, call your local Poison Control Center or go to the nearest emergency room right away.

What should I avoid while taking KEPPRA?
Do not drive, operate machinery or do other dangerous activities until you know how KEPPRA affects you. KEPPRA may make you dizzy or sleepy.

What are the possible side effects of KEPPRA?
KEPPRA can cause serious side effects including:

- See " What is the most important information I should know about KEPPRA?"

Call your healthcare provider right away if you have any of these symptoms:

- mood and behavior changes such as aggression, agitation, anger, anxiety, apathy, mood swings, depression, hostility, and irritability. A few people may get psychotic symptoms such as hallucinations (seeing or hearing things that are really not there), delusions (false or strange thoughts or beliefs) and unusual behavior.
- extreme sleepiness, tiredness, and weakness
- allergic reactions such as swelling of the face, lips, eyes, tongue, and throat, trouble swallowing or breathing, and hives.
- a skin rash. Serious skin rashes can happen after you start taking KEPPRA. There is no way to tell if a mild rash will become a serious reaction.
- a serious allergic reaction that may affect your skin or other parts of your body such as your liver, kidneys, heart, or blood cells. This allergic reaction can be life-threatening and can cause death, particularly if it is not treated as early as possible. Call your healthcare provider right away if you have:

- a skin rash
- swelling of your face
- dark urine

- fever or swollen glands that do not go away
- shortness of breath
- yellowing of the skin or whites of the eyes

- problems with muscle coordination (problems walking and moving)

The most common side effects seen in people who take KEPPRA include:

- sleepiness
- infection

- weakness
- dizziness

The most common side effects seen in children who take KEPPRA include, in addition to those listed above include:

- tiredness
- decreased appetite
- irritability

- acting aggressive
- nasal congestion

Tell your healthcare provider if you have any side effect that bothers you or that does not go away.
These are not all the possible side effects of KEPPRA. For more information, ask your healthcare provider or pharmacist.
Call your doctor for medical advice about side effects. You may report side effects to FDA at 1-800-FDA-1088.

How should I store KEPPRA?

- Store KEPPRAat room temperature, between 59°F to 86°F (15°C to 30°C) away from heat and light.
- Keep KEPPRA and all medicines out of the reach of children.

General information about the safe and effective use of KEPPRA.
Medicines are sometimes prescribed for purposes other than those listed in a Medication Guide. Do not use KEPPRA for a condition for which it was not prescribed. Do not give KEPPRA to other people, even if they have the same symptoms that you have. It may harm them. You can ask your pharmacist or healthcare provider information about KEPPRA that is written for health professionals.

What are the ingredients in KEPPRA?
KEPPRA tabletactive ingredient :levetiracetam
Inactive ingredients: colloidal silicon dioxide, croscarmellose sodium, magnesium stearate, polyethylene glycol 3350, polyethylene glycol 6000, polyvinyl alcohol, talc, titanium dioxide, and additional agents listed below:
250 mg tablets: FD&C Blue #2/indigo carmine aluminum lake
500 mg tablets: iron oxide yellow
750 mg tablets: FD&C yellow #6/sunset yellow FCF aluminum lake, iron oxide red
KEPPRA oral solutionactive ingredient: levetiracetam
Inactive ingredients: ammonium glycyrrhizinate, citric acid monohydrate, glycerin, maltitol solution, methylparaben, potassium acesulfame, propylparaben, purified water, sodium citrate dihydrate and natural and artificial flavor.
KEPPRA does not contain lactose or gluten. KEPPRA oral solution does contain carbohydrates. The liquid is dye-free.
Distributed by
UCB, Inc.
Smyrna, GA 30080
KEPPRA is a registered trademark of the UCB Group of companies
© 2024, UCB, Inc., Smyrna, GA 30080
All rights reserved.
For more information, go to www.keppra.com or call 1-844-599-2273.

This Medication Guide has been approved by the U.S. Food and Drug Administration. Revised: 3/2024

PRINCIPAL DISPLAY PANEL - 250 mg Tablet Bottle Label

NDC 50474-594-40
120 tablets

Keppra®
(levetiracetam)

250 mg tablets

Dispense accompanying
Medication Guide to
each patient.

Rx only

PRINCIPAL DISPLAY PANEL - 500 mg Tablet Bottle Label

NDC 50474-595-40
120 tablets

Keppra®
(levetiracetam)

500 mg tablets

Dispense accompanying
Medication Guide to
each patient.

Rxonly

PRINCIPAL DISPLAY PANEL - 750 mg Tablet Bottle Label

NDC 50474-596-40
120 tablets

Keppra®
(levetiracetam)

750 mg tablets

Dispense accompanying
Medication Guide to
each patient.

Rxonly

PRINCIPAL DISPLAY PANEL - 1000 mg Tablet Bottle Label

NDC 50474-597-66
60 tablets

Keppra®
(levetiracetam)

1000 mg tablets

Dispense accompanying
Medication Guide to
each patient.

Rxonly

PRINCIPAL DISPLAY PANEL - 473 mL Bottle Label

NDC 50474-001-48

Keppra®
(levetiracetam)
100 mg/mL oral solution

Dispense accompanying
Medication Guide to each
patient.

Rx only

16 fl oz (473 mL)